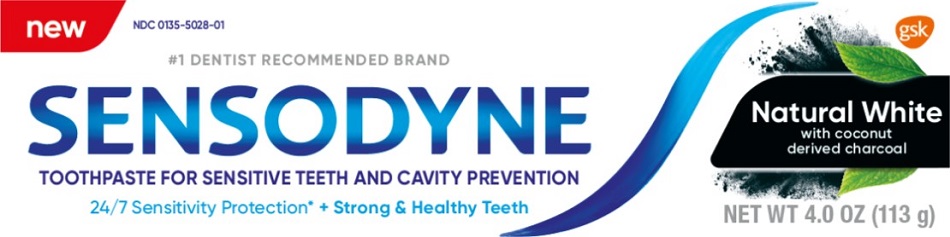 DRUG LABEL: Sensodyne

NDC: 0135-5028 | Form: PASTE
Manufacturer: Haleon US Holdings LLC
Category: otc | Type: HUMAN OTC DRUG LABEL
Date: 20240304

ACTIVE INGREDIENTS: POTASSIUM NITRATE 50 mg/1 g; SODIUM FLUORIDE 1.15 mg/1 g
INACTIVE INGREDIENTS: WATER; SORBITOL; HYDRATED SILICA; GLYCERIN; ACTIVATED CHARCOAL; COCAMIDOPROPYL BETAINE; XANTHAN GUM; SACCHARIN SODIUM; SODIUM HYDROXIDE; SUCRALOSE

Drug Facts

Active ingredients

Potassium nitrate 5%

Sodium fluoride 0.25% (0.15% w/v fluoride ion)

Purposes

Antihypersensitivity

Anticavity

Uses

- builds increasing protection against painful sensitivity of the teeth to cold, heat, acids, sweets, or contact.
- aids in the prevention of dental cavities.

Warnings

Stop use and ask a dentist if

- the problem persists or worsens. Sensitive teeth may indicate a serious problem that may need prompt care by a dentist.
- pain/sensitivity still persists after 4 weeks of use.

Keep out of reach of children.

If more than used for brushing is accidentally swallowed, get medical help or contact a Poison Control Center right away.

Directions

- adults and children 12 years of age and older:
  - apply at least a 1-inch strip of the product onto a soft bristle toothbrush.
  - brush teeth thoroughly for at least 1 minute twice a day (morning and evening), and not more than 3 times a day, or as recommended by a dentist or doctor. Make sure to brush all sensitive areas of the teeth. Minimize swallowing. Spit out after brushing.
- children under 12 years:Consult a dentist or doctor.

Other information

- do not store above 25°C (77°F)

Inactive ingredients

water, sorbitol, hydrated silica, glycerin, charcoal powder, flavor, cocamidopropyl betaine, xanthan gum, sodium saccharin, sodium hydroxide, sucralose

Questions or comments?

1-866-844-2797

Additional Information

ALWAYS FOLLOW THE LABEL

What are sensitive teeth?
Lots of people have sensitive teeth. When enamel is worn away (through eating everyday acidic food or drinks) or gums recede, the dentin underneath becomes exposed. This can lead to tooth sensitivity, for example, with cold and hot food and drinks.

What does Sensodyne do?

Sensodyne provides daily care for sensitive teeth* plus all the benefits you would expect from a daily fluoride toothpaste - strong teeth and freshness.

The active ingredient in Sensodyne is clinically proven to deliver 24/7 sensitivity protection*

Also contains:

Coconut derived charcoal to help restore teeth to their natural whiteness

Use Sensodyne Natural White twice daily:

- Long-lasting sensitivity protection*
- Contains fluoride to protect against cavities
- Helps remove stains for whiter teeth
- Freshens breath

*with twice daily brushing

Trademarks are owned by or licensed to the GSK group of companies.

©2021 GSK group of companies or its licensor.

Distributed by:

GSK Consumer Healthcare

Warren, NJ 07059

Principal Display Panel

NDC 0135-5028-01

new

#1 DENTIST RECOMMENDED BRAND

SENSODYNE

TOOTHPASTE FOR SENSITIVE TEETH AND CAVITY PREVENTION

24/7 Sensitivity Protection* + Strong & Healthy Teeth

Natural White

with coconut derived charcoal

NET WT 4.0 OZ (113 g)

1001361 Carton Front